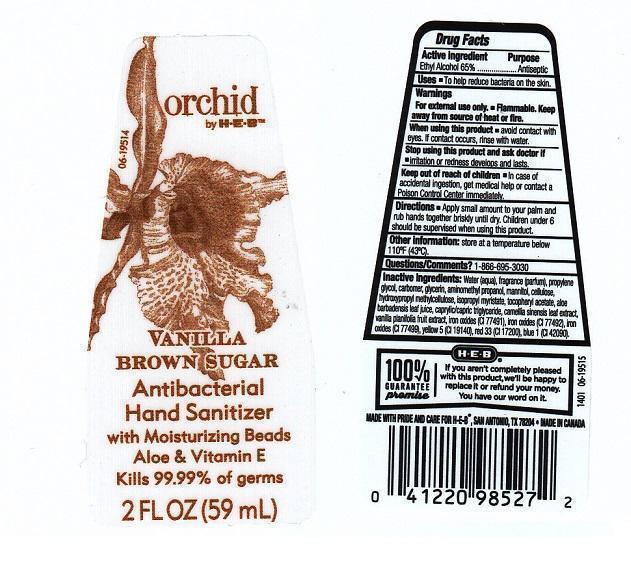 DRUG LABEL: ORCHID BY H E B
NDC: 37808-405 | Form: LIQUID
Manufacturer: H E B
Category: otc | Type: HUMAN OTC DRUG LABEL
Date: 20140304

ACTIVE INGREDIENTS: ALCOHOL 650 mg/1 mL
INACTIVE INGREDIENTS: WATER; PROPYLENE GLYCOL; CARBOMER 934; GLYCERIN; AMINOMETHYLPROPANOL; MANNITOL; POWDERED CELLULOSE; HYPROMELLOSES; ISOPROPYL MYRISTATE; .ALPHA.-TOCOPHEROL ACETATE; ALOE VERA LEAF; MEDIUM-CHAIN TRIGLYCERIDES; GREEN TEA LEAF; VANILLA; FERRIC OXIDE RED; FERRIC OXIDE YELLOW; FERROSOFERRIC OXIDE; FD&C YELLOW NO. 5; D&C RED NO. 33; FD&C BLUE NO. 1

DRUG FACTS

ACTIVE INGREDIENT

ETHYL ALCOHOL 65%

PURPOSE

ANTISEPTIC

USES

TO HELP REDUCE BACTERIA ON THE SKIN

WARNINGS

FOR EXTERNAL USE ONLY. FLAMMABLE. KEEP AWAY FROM SOURCE OF HEAT OR FIRE

WHEN USING THIS PRODUCT

AVOID CONTACT WITH EYES. IF CONTACT OCCURS, RINSE WITH WATER

STOP USING THIS PRODUCT AND ASK DOCTOR IF

IRRITATION OR REDNESS DEVELOPS AND LASTS

KEEP OUT OF REACH OF CHILDREN

IN CASE OF ACCIDENTAL INGESTION, GET MEDICAL HELP OR CONTACT A POISON CONTROL CENTER IMMEDIATELY

DIRECTIONS

APPLY A SMALL AMOUNT TO YOUR PALM AND RUB HANDS TOGETHER BRISKLY UNTIL DRY. CHILDREN UNDER 6 SHOULD BE SUPERVISED WHEN USING THIS PRODUCT

OTHER INFORMATION

STORE AT A TEMPERATURE BELOW 110°F (43°C)

QUESTIONS/COMMENTS?

1-866-695-3030

INACTIVE INGREDIENTS

WATER (AQUA), FRAGRANCE (PARFUM), PROPYLENE GLYCOL, CARBOMER, GLYCERIN, AMINOMETHYL PROPANOL, MANNITOL, CELLULOSE, HYDROXYPROPYL METHYLCELLULOSE, ISOPROPYL MYRISTATE, TOCOPHERYL ACETATE, ALOE BARBADENSIS LEAF JUICE, CAPRYLIC/CAPRIC TRIGLYCERIDE, CAMELLIA SINENSIS LEAF EXTRACT, VANILLA PLANIFOLIA FRUIT EXTRACT, IRON OXIDES (CI 77491), IRON OXIDES (CI 77492), IRON OXIDES (CI 77499), YELLOW 5 (CI 19140), RED 33 (CI 17200), BLUE 1 (CI 42090)